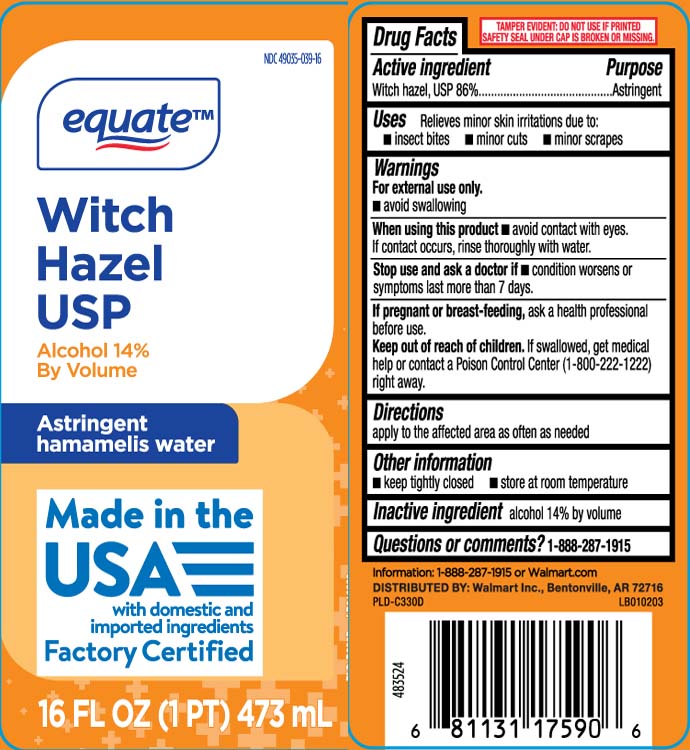 DRUG LABEL: Witch Hazel
NDC: 49035-039 | Form: LIQUID
Manufacturer: EQUATE (Wal-Mart Stores, Inc.) (see also WAL-MART INC)
Category: otc | Type: HUMAN OTC DRUG LABEL
Date: 20260204

ACTIVE INGREDIENTS: WITCH HAZEL 842 mg/1 mL
INACTIVE INGREDIENTS: ALCOHOL

Drug Facts

Active ingredient

Witch hazel, USP 86%

Purpose

Astringent

Uses

Relieves minor skin irritation due to:

- insect bites
- minor cuts
- minor scrapes

Warnings

For external use only.

- Avoid swallowing.

When using this product

avoid contact with eyes. If contact occurs, rinse thoroughly with water.

Stop use and ask a doctor if

condition worsens or symptoms persist for more than 7 days

If pregnant or breast-feeding,

ask a health professional before use.

Keep out of reach of children.

If swallowed, get medical help or contact a Poison Control Center (1-800-222-1222) right away.

Directions

apply to the affected area as often as needed

Other information

- keep tightly closed
- store at room temperature

Inactive ingredient

alcohol 14% by volume

Questions or comments?

Call 1-888-287-1915

Principal Display Panel

Witch Hazel USP

Alcohol 14% By Volume

Astringent

hamamelis water

FL OZ (mL)

TAMPER EVIDENT: DO NOT USE IF PRINTED SAFETY SEAL UNDER CAP IS BROKEN OR MISSING.

DISTRIBUTED BY: Walmart Inc., Bentonville, AR 72716

Package Label

EQUATE Witch Hazel